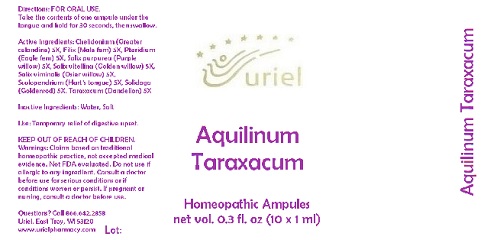 DRUG LABEL: Aquilinum Taraxacum Ampules
NDC: 48951-1285 | Form: LIQUID
Manufacturer: Uriel Pharmacy Inc.
Category: homeopathic | Type: HUMAN OTC DRUG LABEL
Date: 20180502

ACTIVE INGREDIENTS: DRYOPTERIS FILIX-MAS ROOT 5 [hp_X]/1 mL; PTERIDIUM AQUILINUM WHOLE 5 [hp_X]/1 mL; CHELIDONIUM MAJUS 5 [hp_X]/1 mL; TARAXACUM PALUSTRE ROOT 5 [hp_X]/1 mL; SALIX ALBA FLOWER 5 [hp_X]/1 mL; SOLIDAGO VIRGAUREA FLOWERING TOP 5 [hp_X]/1 mL; SALIX PURPUREA BARK 5 [hp_X]/1 mL; WILLOW BARK 5 [hp_X]/1 mL; ASPLENIUM SCOLOPENDRIUM TOP 5 [hp_X]/1 mL
INACTIVE INGREDIENTS: SODIUM CHLORIDE; WATER

Aquilinum Taraxacum

INDICATIONS AND USAGE

Directions: FOR ORAL USE.

DOSAGE AND ADMINISTRATION

Take the contents of one ampule under the tongue and hold for 30 seconds, then swallow.

ACTIVE INGREDIENT

Active Ingredients: Chelidonium (Greater celandine) 5X, Filix (Male fern) 5X, Pteridium (Eagle fern) 5X, Salix purpurea (Purple willow) 5X, Salix vitellina (Golden willow) 5X, Salix viminalis (Osier willow) 5X, Scolopendrium (Hart’s tongue) 5X, Solidago (Goldenrod) 5X, Taraxacum (Dandelion) 5X

Inactive Ingredients: Water, Salt

PURPOSE

Use: Temporary relief of digestive upset.

KEEP OUT OF REACH OF CHILDREN.

WARNINGS

Warnings: Claims based on traditional homeopathic practice, not accepted medical evidence. Not FDA evaluated. Do not use if allergic to any ingredient. Consult a doctor before use for serious conditions or if conditions worsen or persist. If pregnant or nursing, consult a doctor before use.

Questions? Call 866.642.2858
Uriel, East Troy, WI 53120
www.urielpharmacy.com